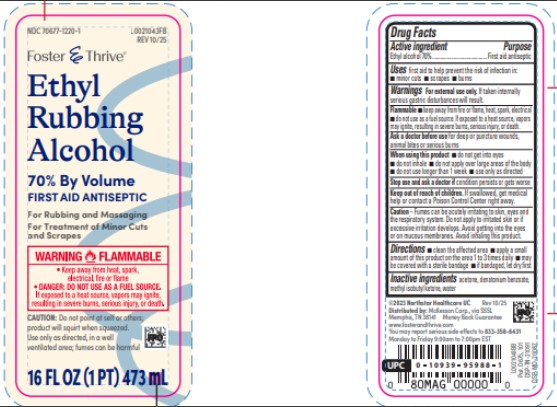 DRUG LABEL: Ethyl alcohol
NDC: 70677-1220 | Form: LIQUID
Manufacturer: Strategic Sourcing Services LLC
Category: otc | Type: HUMAN OTC DRUG LABEL
Date: 20260217

ACTIVE INGREDIENTS: ALCOHOL 70 mL/100 mL
INACTIVE INGREDIENTS: ACETONE; DENATONIUM BENZOATE; METHYL ISOBUTYL KETONE; WATER

Foster & Thrive 876.002/876AC
70% Ethyl Rubbing Alcohol

Active ingredient

Ethyl alcohol 70%

Purpose

First aid antiseptic

Uses

first aid to help prevent the risk of infection in:

- minor cuts
- scrapes
- burns

Warnings

For external use only. If taken internally serious gastric disturbances will result.

Flammable

- keep away from fire or flame, heatm spark, electrical
- do not use as a fuel source. If exposed to a heat source, vapors may ignite, resulting in severe burns, serious injury, or death.

Ask a doctor before use

for deep or puncture wounds, animal bites or serious burns

When using this product

- do not get into eyes
- do not inhale
- do not apply over large areas of the body
- do not use longer than 1 week
- use only as directed

Stop use and ask a doctor if

condition persists or gets worse

Keep out of reach of children.

If swallowed, get medical help or contact a Poison Control Center right away.

Caution

Fumes can be acutely irritating to skin, eyes and the respiratory system. Do not apply to irritated skin or if excessive irritation develops. Avoid getting into the eyes or on mucous membranes. Avoid inhaling this product.

Directions

- clean the affected area
- apply a small amount of this product on the area 1 to 3 times daily
- may be covered with a sterile bandage
- if bandaged, let dry first

Inactive ingredients

acetone, denatonium benzoate, methyl isobutyl ketone, water

Adverse event

© 2025 Northstar Healthcare LLC

Distributed by: McKesson Corp., via SSSL

Memphis, TN 38141 Money Back Guarantee

www.fosterandthrive.com

You may report serious side effects to 833-358-6431

Monday to Friday 9:00am to 7:00pm EST

Pat. D675, 101

DSP-TN-21091

DSP-MO-20087

Principal panel display

NDC 70677-1220-1

Foster & Thrive™

Ethyl Rubbing Alcohol

70% By Volume

FIRST AID ANTISEPTIC

For Rubbing and Massaging

For Treatment of Minor Cuts and Scrapes

WARNING FLAMMABLE

- Keep away from heat, spark, electrical, fire or flame
- DANGER: DO NOT USE AS A FUEL SOURCE.If exposed to a heat source, vapors may ignite, resulting in severe burns, serious injury, or death.

CAUTION: Do not point at self or others; product will squirt when squeezed.

Use only as directed, in a well-ventilated area; fumes can be harmful

16 FL OZ (1 PT) 473 mL